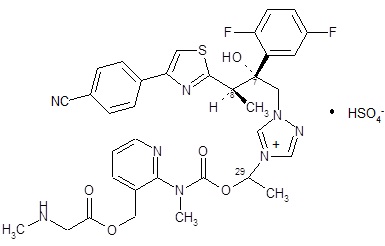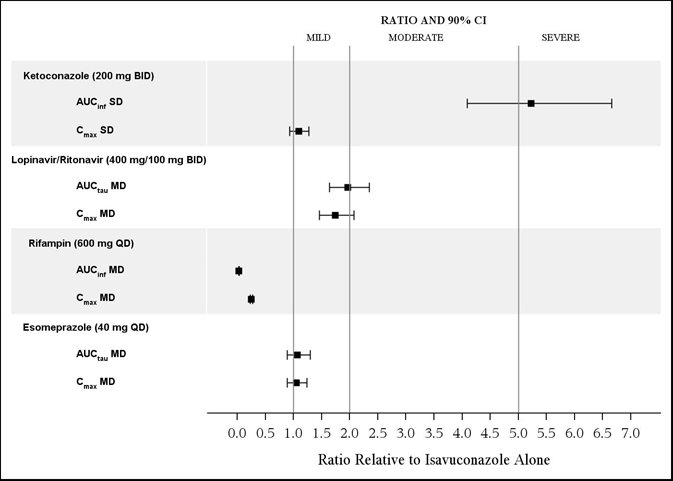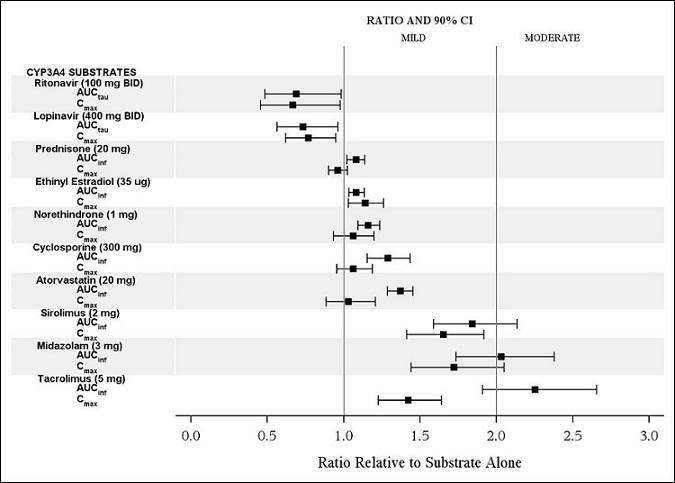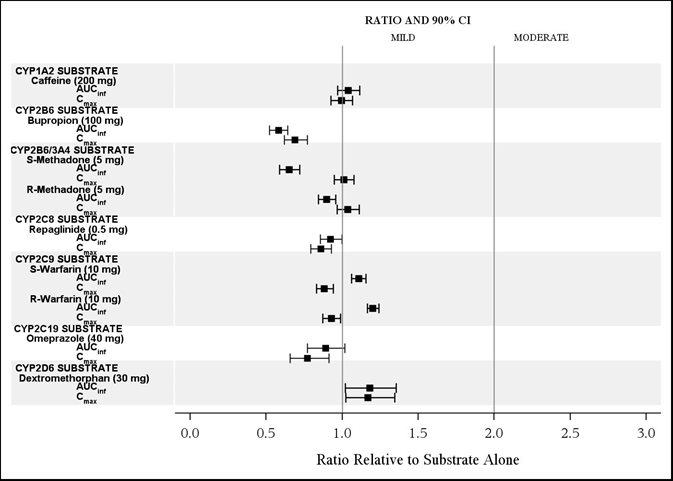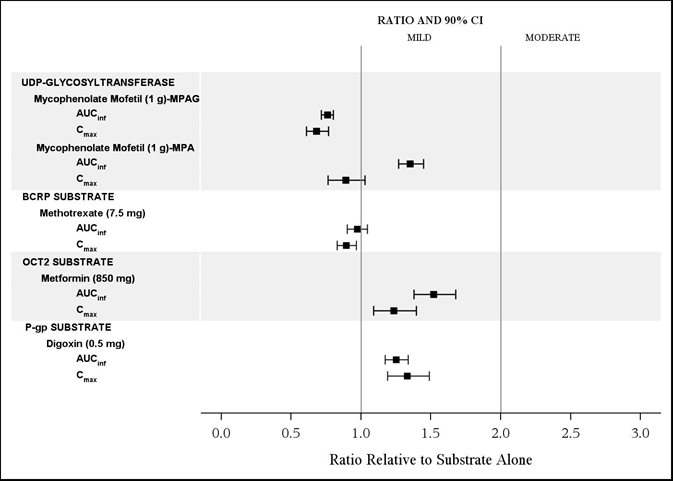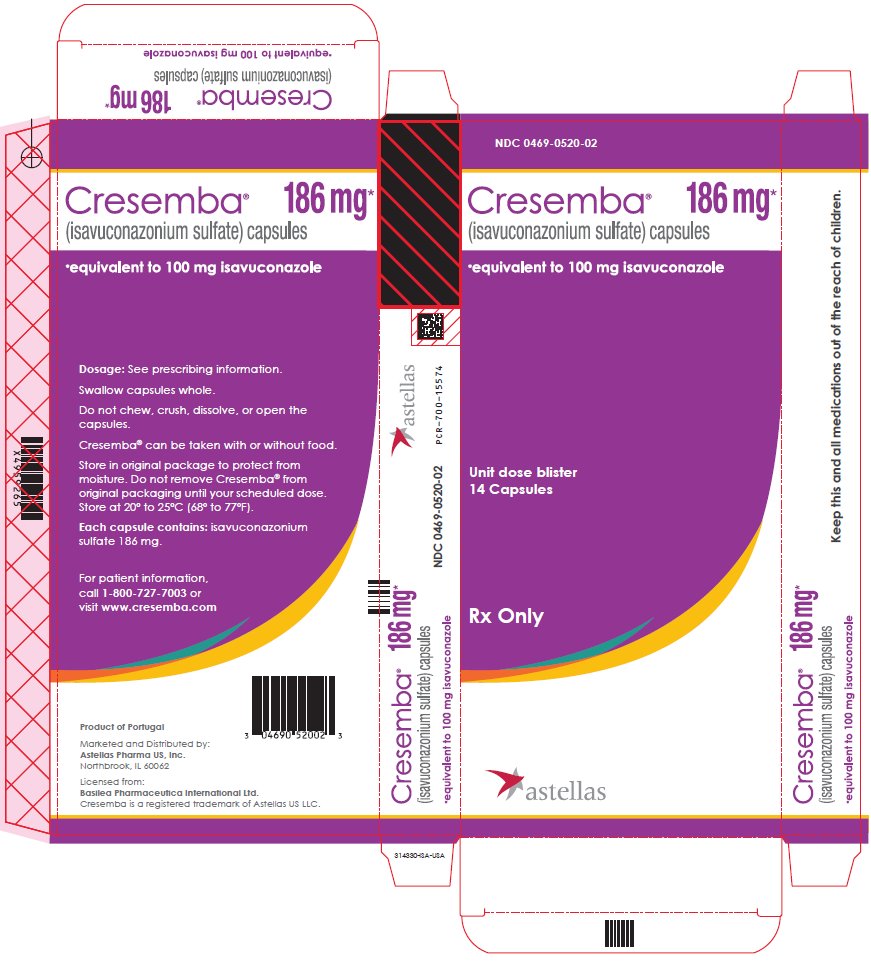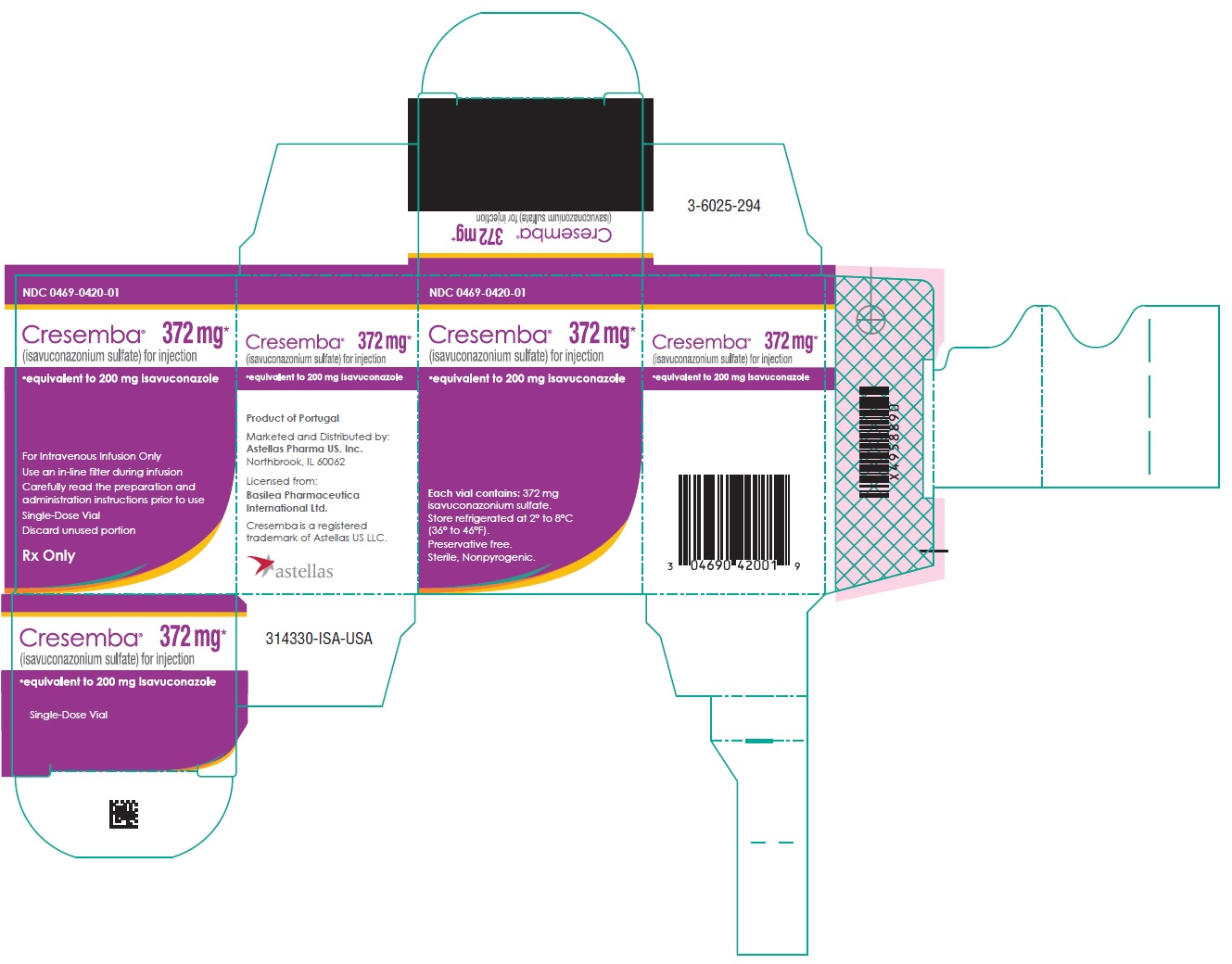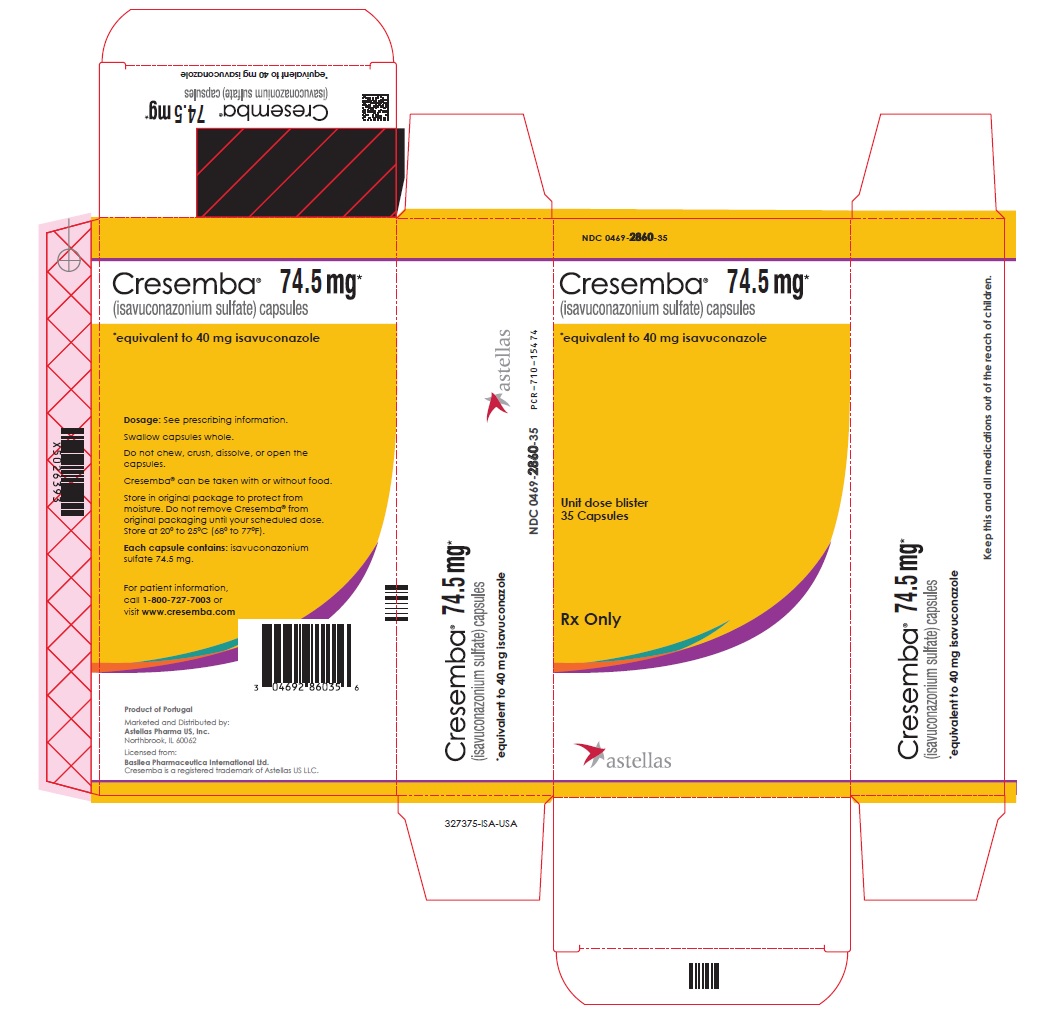 DRUG LABEL: CRESEMBA
NDC: 0469-0520 | Form: CAPSULE
Manufacturer: Astellas Pharma US, Inc.
Category: prescription | Type: HUMAN PRESCRIPTION DRUG LABEL
Date: 20250425

ACTIVE INGREDIENTS: ISAVUCONAZONIUM SULFATE 100 mg/1 1

HIGHLIGHTS OF PRESCRIBING INFORMATION

These highlights do not include all the information needed to use CRESEMBA® safely and effectively. See full prescribing information for CRESEMBA®.
CRESEMBA® (isavuconazonium sulfate) capsules, for oral use
CRESEMBA® (isavuconazonium sulfate) for injection, for intravenous use
Initial U.S. Approval: 2015

1 INDICATIONS AND USAGE

CRESEMBA® is an azole antifungal indicated for the treatment of:

Invasive aspergillosis (1.1) and Invasive mucormycosis (1.2) as follows:

- CRESEMBA for injection: adults and pediatric patients 1 year of age and older
- CRESEMBA capsules: adults and pediatric patients 6 years of age and older who weigh 16 kilograms (kg) and greater

2 DOSAGE AND ADMINISTRATION

Important Administration Instructions:

- CRESEMBA for injection is intended for use in patients who are 1 year of age and older (2.1, 2.3).
- CRESEMBA for injection via nasogastric (NG) tube administration is intended for use by patients who are 6 years of age and older and weighing 16 kg and greater. (2.1, 2.6).
- CRESEMBA for injection must be administered through an in-line filter over a minimum of 1 hour. (2.1, 2.5).
- CRESEMBA capsules are intended for use in patients who are 6 years of age and older and weighing 16 kg and greater (2.1, 2.3).
- CRESEMBA capsules can be taken with or without food. (2.1).

Recommended Dosage in Adult Patients (2.2):

Recommended Dosage for CRESEMBA in Adult Patients (2.2)
Dosage Form | Loading Dose | Maintenance Dose [Start maintenance doses 12 to 24 hours after the last loading dose]
CRESEMBA for Injection, 372 mg/vial; 372 mg of isavuconazonium sulfate per vial | One reconstituted vial (372 mg); intravenously; every 8 hours for 6 doses (48 hours) | One reconstituted vial (372 mg); intravenously; once daily
CRESEMBA Capsules, 186 mg; 186 mg of isavuconazonium sulfate per capsule | Two 186 mg capsules (372 mg); orally; every 8 hours for 6 doses (48 hours) | Two 186 mg capsules (372 mg); orally; once daily
CRESEMBA Capsules, 74.5 mg; 74.5 mg of isavuconazonium sulfate per capsule | Five 74.5 mg capsules (372 mg); orally; every 8 hours for 6 doses (48 hours) | Five 74.5 mg capsules (372 mg); orally; once daily

Recommended Dosage in Pediatric Patients (2.3):

- The maximum of any individual loading or daily maintenance dose to be administered to any pediatric patient is 372 mg of CRESEMBA. (2.3)

Recommended Dosage for CRESEMBA in Pediatric Patients (2.3)
Dosage Form | Age | Body Weight (kg) | Loading Dose | Maintenance Dose [Start maintenance doses 12 to 24 hours after the last loading dose]
CRESEMBA for Injection, 372 mg/vial; 372 mg of isavuconazonium sulfate per vial | 1 to less than 3 years of age | less than 18 kg | 15 mg/kg; intravenously; every 8 hours for 6 doses (48 hours) | 15 mg/kg; intravenously; once daily
CRESEMBA for Injection, 372 mg/vial; 372 mg of isavuconazonium sulfate per vial | 3 to less than 18 years of age | less than 37 kg | 10 mg/kg; intravenously; every 8 hours for 6 doses (48 hours) | 10 mg/kg; intravenously; once daily
CRESEMBA for Injection, 372 mg/vial; 372 mg of isavuconazonium sulfate per vial | 3 to less than 18 years of age | greater than or equal to 37 kg | One reconstituted vial (372 mg); intravenously; every 8 hours for 6 doses (48 hours) | One reconstituted vial (372 mg); intravenously; once daily
CRESEMBA Capsules, 74.5 mg; 74.5 mg of isavuconazonium sulfate per capsule | 6 to less than 18 years of age | 16 kg to less than 18 kg | Two capsules (149 mg); orally; every 8 hours for 6 doses (48 hours) | Two capsules (149 mg); orally; once daily
CRESEMBA Capsules, 74.5 mg; 74.5 mg of isavuconazonium sulfate per capsule | 6 to less than 18 years of age | 18 kg to less than 25 kg | Three capsules (223.5 mg); orally; every 8 hours for 6 doses (48 hours) | Three capsules (223.5 mg); orally; once daily
CRESEMBA Capsules, 74.5 mg; 74.5 mg of isavuconazonium sulfate per capsule | 6 to less than 18 years of age | 25 kg to less than 32kg | Four capsules (298 mg); orally; every 8 hours for 6 doses (48 hours) | Four capsules (298 mg); orally; once daily
CRESEMBA Capsules, 74.5 mg; 74.5 mg of isavuconazonium sulfate per capsule | 6 to less than 18 years of age | greater than or equal to 32 kg | Five 74.5 mg capsules (372 mg); orally; every 8 hours for 6 doses (48 hours) | Five 74.5 mg capsules (372 mg); orally; once daily

3 DOSAGE FORMS AND STRENGTHS

- CRESEMBA for injection is supplied in a single-dose vial as a sterile lyophilized powder containing 372 mg of isavuconazonium sulfate (equivalent to 200 mg of isavuconazole). (3)
- CRESEMBA capsules: 74.5 mg of isavuconazonium sulfate (equivalent to 40 mg of isavuconazole), 186 mg of isavuconazonium sulfate (equivalent to 100 mg of isavuconazole). (3)

4 CONTRAINDICATIONS

- Hypersensitivity to CRESEMBA. (4)
- Coadministration with strong CYP3A4 inhibitors, such as ketoconazole or high-dose ritonavir. (4, 7)
- Coadministration with strong CYP3A4 inducers, such as rifampin, carbamazepine, St. John’s wort, or long acting barbiturates. (4, 7)
- Use in patients with familial short QT syndrome. (4)

5 WARNINGS AND PRECAUTIONS

- Hepatic Adverse Drug Reactions: Serious hepatic reactions have been reported. Evaluate liver-related laboratory tests at the start and during the course of CRESEMBA therapy. (5.1)
- Infusion-related reactions were reported during intravenous administration of CRESEMBA. Discontinue the infusion if these reactions occur. (5.2)
- Hypersensitivity Reactions: Anaphylactic reactions, with fatal outcome, have been reported during treatment with CRESEMBA. Serious skin reactions, such as Stevens-Johnson syndrome, have been reported during treatment with other azole antifungal agents. Discontinue CRESEMBA if anaphylactic or serious skin reactions occur, and initiate supportive treatment as needed. (5.3)
- Embryo-Fetal Toxicity: CRESEMBA may cause fetal harm when administered to a pregnant woman. Advise pregnant women of the potential risk to the fetus. Advise females of reproductive potential to use an effective method of contraception. (5.4, 8.1, 8.3)
- Drug Interactions: Review patient’s concomitant medications. Several drugs may significantly alter isavuconazole concentrations. Isavuconazole may alter concentrations of several drugs. (5.5, 7, 12.3)
- Drug Particulates: Intravenous formulation may form insoluble particulates following reconstitution. Administer CRESEMBA through an in-line filter. (2.4, 5.6)

6 ADVERSE REACTIONS

- Adult Patients: The most frequent adverse reactions in adult patients were nausea, vomiting, diarrhea, headache, elevated liver chemistry tests, hypokalemia, constipation, dyspnea, cough, peripheral edema, and back pain. (6.1)
- Pediatric Patients: The most frequent adverse reactions in pediatric patients were diarrhea, abdominal pain, vomiting, elevated liver chemistry tests, rash, nausea, pruritus, and headache. (6.1)

To report SUSPECTED ADVERSE REACTIONS, contact Astellas Pharma US, Inc. at 1-800-727-7003 or FDA at 1-800-FDA-1088 or www.fda.gov/medwatch.

7 DRUG INTERACTIONS

- CYP3A4 inhibitors or inducers may alter the plasma concentrations of isavuconazole. (7)
- Appropriate therapeutic drug monitoring and dose adjustment of immunosuppressants (i.e., tacrolimus, sirolimus, and cyclosporine) may be necessary when coadministered with CRESEMBA. (7)
- Drugs with a narrow therapeutic window that are P-gp substrates, such as digoxin, may require dose adjustment when administered concomitantly with CRESEMBA. (7)

8 USE IN SPECIFIC POPULATIONS

- Breastfeeding should be discontinued during treatment with CRESEMBA. (8.2)
- Use in patients with severe hepatic impairment only when the benefits outweigh the risks; clinical monitoring for CRESEMBA‑related adverse reactions is recommended. (8.7)

FULL PRESCRIBING INFORMATION

1 INDICATIONS AND USAGE

1.1 Invasive Aspergillosis

CRESEMBA® is indicated for the treatment of invasive aspergillosis as follows:

CRESEMBA for injection: adults and pediatric patients 1 year of age and older [see Clinical Studies (14.1) and Clinical Pharmacology (12.4)]

CRESEMBA capsules: adults and pediatric patients 6 years of age and older who weigh 16 kilograms (kg) and greater [see Dosage and Administration (2.3) Clinical Studies (14.1) and Clinical Pharmacology (12.4)]

1.2 Invasive Mucormycosis

CRESEMBA is indicated for the treatment of invasive mucormycosis as follows:

CRESEMBA for injection: adults and pediatric patients 1 year of age and older [see Clinical Studies (14.1) and Clinical Pharmacology (12.3, 12.4)]

CRESEMBA capsules: adults and pediatric patients 6 years of age and older who weigh 16 kg and greater [see Dosage and Administration (2.3)], Clinical Studies (14.1) and Clinical Pharmacology (12.3, 12.4)]

1.3 Usage

Specimens for fungal culture and other relevant laboratory studies (including histopathology) to isolate and identify causative organism(s) should be obtained prior to initiating antifungal therapy. Therapy may be instituted before the results of the cultures and other laboratory studies are known. However, once these results become available, antifungal therapy should be adjusted accordingly.

2 DOSAGE AND ADMINISTRATION

2.1 Important Administration Instructions for CRESEMBA

CRESEMBA for Injection

- CRESEMBA for injection is intended for use in patients who are 1 year of age and older [see Dosage and Administration (2.2 and 2.3)].
- Intravenous formulation must be administered via an infusion set with an in-line filter (pore size 0.2 to 1.2 micron).
- Infuse the intravenous formulation over a minimum of 1 hour in 250 mL of a compatible diluent, to reduce the risk for infusion-related reactions. Do not administer as an intravenous bolus injection.
- Do not infuse CRESEMBA with other intravenous medications.
- Flush intravenous lines with 0.9% sodium chloride injection, USP or 5% dextrose injection, USP prior to and after infusion of CRESEMBA.
- After dilution of the intravenous formulation, avoid unnecessary vibration or vigorous shaking of the solution. Do not use a pneumatic transport system.

Nasogastric Tube Administration of CRESEMBA for Injection

- CRESEMBA for injection via nasogastric (NG) tube administration is intended for use by patients who are 6 years of age and older and weighing 16 kg and greater [see Dosage and Administration (2.2, 2.3 and 2.6].

CRESEMBA Capsules

- CRESEMBA capsules are intended for use in patients who are 6 years of age and older and weighing 16 kg and greater [see Dosage and Administration (2.2 and 2.3)].
- Switching between the intravenous and oral formulations of CRESEMBA is acceptable as bioequivalence has been demonstrated. Loading dose is not required when switching between formulations.
- With oral administration, swallow CRESEMBA capsules whole. Do not chew, crush, dissolve, or open the capsules. CRESEMBA capsules can be taken with or without food.

2.2 Recommended Dosage and Administration in Adult Patients

Recommended dosage and administration of CRESEMBA for injection and capsules in adult patients is described in Table 1 below. CRESEMBA (isavuconazonium sulfate) is the prodrug of isavuconazole, an azole antifungal drug.

Table 1. Recommended Dosage and Administration for CRESEMBA in Adult Patients
Dosage Form | Loading Dose | Maintenance Dose [Start maintenance doses 12 to 24 hours after the last loading dose.]
CRESEMBA for Injection, 372 mg/vial; 372 mg [372 mg of isavuconazonium sulfate is equivalent to 200 mg of isavuconazole.] of isavuconazonium sulfate per vial | One reconstituted vial (372 mg); intravenously; every 8 hours for 6 doses (48 hours) | One reconstituted vial (372 mg); intravenously; once daily
CRESEMBA Capsules,; 186 mg; 186 mg [186 mg of isavuconazonium sulfate is equivalent to 100 mg of isavuconazole.] of isavuconazonium sulfate per capsule | Two 186 mg capsules (372 mg); orally; every 8 hours for 6 doses (48 hours) | Two 186 mg capsules (372 mg); orally; once daily
CRESEMBA Capsules, 74.5 mg; 74.5 mg [74.5 mg of isavuconazonium sulfate is equivalent to 40 mg of isavuconazole.] of isavuconazonium sulfate per capsule | Five 74.5 mg capsules (372 mg); orally; every 8 hours for 6 doses (48 hours) | Five 74.5 mg capsules (372 mg); orally; once daily

2.3 Recommended Dosage and Administration in Pediatric Patients

Recommended dosage and administration of CRESEMBA for injection and CRESEMBA capsules in pediatric patients is described in Table 2 below [see Clinical Pharmacology (12.3)]. The maximum of any individual loading or daily maintenance dose to be administered to any pediatric patient is 372 mg of CRESEMBA.

Table 2. Recommended Dosage and Administration for CRESEMBA in Pediatric Patients
Dosage Form | Age | Body Weight (kg) | Loading Dose | Maintenance Dose [Start maintenance doses 12 to 24 hours after the last loading dose.]
CRESEMBA for Injection,; 372 mg/vial; 372 mg [372 mg of isavuconazonium sulfate is equivalent to 200 mg of isavuconazole.] of isavuconazonium sulfate per vial | 1 year to less than 3 years of age | less than 18 kg | 15 mg/kg; intravenously; every 8 hours for 6 doses (48 hours) | 15 mg/kg; intravenously; once daily
CRESEMBA for Injection,; 372 mg/vial; 372 mg [372 mg of isavuconazonium sulfate is equivalent to 200 mg of isavuconazole.] of isavuconazonium sulfate per vial | 3 years to less than 18 years of age | less than 37 kg | 10 mg/kg; intravenously; every 8 hours for 6 doses (48 hours) | 10 mg/kg; intravenously; once daily
CRESEMBA for Injection,; 372 mg/vial; 372 mg [372 mg of isavuconazonium sulfate is equivalent to 200 mg of isavuconazole.] of isavuconazonium sulfate per vial | 3 years to less than 18 years of age | greater than or equal to 37 kg | One reconstituted vial (372 mg); intravenously; every 8 hours for 6 doses (48 hours) | One reconstituted vial (372 mg); intravenously; once daily
CRESEMBA Capsules,; 74.5 mg; 74.5 mg [74.5 mg of isavuconazonium sulfate is equivalent to 40 mg of isavuconazole.] of isavuconazonium sulfate per capsule | 6 to less than 18 years of age | 16 kg to less than 18 kg | Two capsules (149 mg); orally; every 8 hours for 6 doses (48 hours) | Two capsules (149 mg); orally; once daily
CRESEMBA Capsules,; 74.5 mg; 74.5 mg [74.5 mg of isavuconazonium sulfate is equivalent to 40 mg of isavuconazole.] of isavuconazonium sulfate per capsule | 6 to less than 18 years of age | 18 kg to less than 25 kg | Three capsules (223.5 mg); orally; every 8 hours for 6 doses (48 hours) | Three capsules (223.5 mg); orally; once daily
CRESEMBA Capsules,; 74.5 mg; 74.5 mg [74.5 mg of isavuconazonium sulfate is equivalent to 40 mg of isavuconazole.] of isavuconazonium sulfate per capsule | 6 to less than 18 years of age | 25 kg to less than 32 kg | Four capsules (298 mg); orally; every 8 hours for 6 doses (48 hours) | Four capsules (298 mg); orally; once daily
CRESEMBA Capsules,; 74.5 mg; 74.5 mg [74.5 mg of isavuconazonium sulfate is equivalent to 40 mg of isavuconazole.] of isavuconazonium sulfate per capsule | 6 to less than 18 years of age | greater than or equal to 32 kg | Five capsules [Five 74.5 mg CRESEMBA capsules are equivalent to two 186 mg CRESEMBA capsules.] (372 mg); orally; every 8 hours for 6 doses (48 hours) | Five capsules (372 mg); orally; once daily

2.4 Reconstitution Instructions for the CRESEMBA for Injection Formulation

Aseptic technique must be strictly observed in all handling since no preservative or bacteriostatic agent is present in CRESEMBA or in the materials specified for reconstitution. CRESEMBA is water soluble, preservative-free, sterile, and nonpyrogenic.

- Reconstitute one vial of CRESEMBA by adding 5 mL water for injection, USP to the vial. The resultant solution will be 74.4 mg/mL of isavuconazonium sulfate.
- Gently shake to dissolve the powder completely.
- Visually inspect the reconstituted solution for particulate matter and discoloration. Reconstituted CRESEMBA should be clear and free of visible particulate.
- The reconstituted solution may be stored between 5°C to 25°C (41°F to 77°F) for a maximum of 1 hour prior to preparation of the patient intravenous infusion solution [see Dosage and Administration (2.5)].
- For nasogastric tube administration, the reconstituted solution should be administered within 1 hour of reconstitution [see Dosage and Administration (2.6)].
- Discard any unused portion of the reconstituted solution.

2.5 Dilution and Preparation Instructions for the Intravenous Administration of the CRESEMBA for Injection Formulation

- Based on the adult or pediatric dosage regimen [see Dosage and Administration (2.2 and 2.3)], remove the appropriate volume of the reconstituted solution (74.4 mg/mL of isavuconazonium sulfate) from the vial and add it to an infusion bag containing 250 mL of compatible diluent [see Dosage and Administration (2.7)]. A smaller volume infusion bag of compatible diluent may be used as long as the final concentration does not exceed approximately 1.5 mg isavuconazonium sulfate per mL.
- The diluted solution may show visible translucent to white particulates of isavuconazole (which will be removed by in-line filtration).
- Use gentle mixing or roll bag to minimize the formation of particulates. Avoid unnecessary vibration or vigorous shaking of the solution.
- Apply in-line filter with a microporous membrane pore size of 0.2 to 1.2 micron and in-line filter reminder sticker to the infusion bag.
- Do not use a pneumatic transport system.
- The intravenous administration should be completed within 6 hours of dilution at room temperature. If this is not possible, immediately refrigerate (2°C to 8°C / 36°F to 46°F) the infusion solution after dilution and complete the infusion within 24 hours. Do not freeze the infusion solution.

2.6 Preparation Instructions for the Nasogastric Tube Administration of the CRESEMBA for Injection Formulation

CRESEMBA for injection can be administered through a nasogastric tube as follows:

- Utilizing aseptic technique, reconstitute one vial of CRESEMBA for injection (equivalent to 200 mg isavuconazole) with 5 mL of water for injection, USP [see Dosage and Administration (2.4)].
- Based on the adult or pediatric (6 years of age to less than 18 years of age) CRESEMBA for injection dosage regimen [see Dosage and Administration (2.2, 2.3)], withdraw the appropriate volume of the reconstituted solution (74.4 mg/mL of isavuconazonium sulfate) from the vial using an appropriate syringe and needle. Discard the needle and cap the syringe.
- To administer, remove the cap from the syringe containing the reconstituted solution and connect the syringe to the nasogastric (NG) tube to deliver the dose. After administering the dose, administer three 5 mL rinses to the NG tube with water [see Clinical Pharmacology (12.3)].
- Administer the reconstituted solution via the nasogastric tube within 1 hour of reconstitution. Discard any unused portion of the reconstituted solution.
- Do not administer CRESEMBA capsules through a nasogastric tube.

2.7 Compatibility for the Injection Formulation

CRESEMBA for injection should only be administered with the following diluents:

- 0.9% sodium chloride injection, USP
- 5% dextrose injection, USP

3 DOSAGE FORMS AND STRENGTHS

CRESEMBA Capsules

CRESEMBA 74.5 mg isavuconazonium sulfate (equivalent to 40 mg of isavuconazole) capsules are opaque and have a Swedish orange (reddish-brown) body imprinted with the Astellas logo in black ink and a Swedish orange cap imprinted with “557” in black ink.

CRESEMBA 186 mg isavuconazonium sulfate (equivalent to 100 mg of isavuconazole) capsules are opaque, elongated and have a Swedish orange (reddish-brown) body imprinted with the Astellas logo in black ink and a white cap imprinted with “766” in black ink.

CRESEMBA for Injection

Each single-dose vial of CRESEMBA for injection contains 372 mg isavuconazonium sulfate (equivalent to 200 mg of isavuconazole). CRESEMBA for injection is supplied in a single-dose vial as a sterile lyophilized white to yellow powder.

4 CONTRAINDICATIONS

- CRESEMBA is contraindicated in persons with known hypersensitivity to isavuconazole.
- Coadministration of strong CYP3A4 inhibitors, such as ketoconazole or high-dose ritonavir (400 mg every 12 hours), with CRESEMBA is contraindicated because strong CYP3A4 inhibitors can significantly increase the plasma concentration of isavuconazole [see Drug Interactions (7) and Clinical Pharmacology (12.3)].
- Coadministration of strong CYP3A4 inducers, such as rifampin, carbamazepine, St. John’s wort, or long acting barbiturates with CRESEMBA is contraindicated because strong CYP3A4 inducers can significantly decrease the plasma concentration of isavuconazole [see Drug Interactions (7) and Clinical Pharmacology (12.3)].
- CRESEMBA shortened the QTc interval in a concentration-related manner. CRESEMBA is contraindicated in patients with familial short QT syndrome [see Clinical Pharmacology (12.2)].

5 WARNINGS AND PRECAUTIONS

5.1 Hepatic Adverse Drug Reactions

Hepatic adverse drug reactions (e.g., elevations in alanine aminotransferase (ALT), aspartate aminotransferase (AST), alkaline phosphatase, total bilirubin) have been reported in clinical trials. The elevations in liver-related laboratory tests were generally reversible and did not require discontinuation of CRESEMBA. Cases of more severe hepatic adverse drug reactions including hepatitis, cholestasis or hepatic failure including death have been reported in patients with serious underlying medical conditions (e.g., hematologic malignancy) during treatment with azole antifungal agents, including CRESEMBA.

Evaluate liver-related laboratory tests at the start and during the course of CRESEMBA therapy. Monitor patients who develop abnormal liver-related laboratory tests during CRESEMBA therapy for the development of more severe hepatic injury. Discontinue CRESEMBA if clinical signs and symptoms consistent with liver disease develop that may be attributable to CRESEMBA [see Adverse Reactions (6.1)].

5.2 Infusion-Related Reactions

Infusion-related reactions including hypotension, dyspnea, chills, dizziness, paresthesia, and hypoesthesia were reported during intravenous administration of CRESEMBA. Discontinue the infusion if these reactions occur [see Adverse Reactions (6.1)].

5.3 Hypersensitivity Reactions

Anaphylactic Reactions

Anaphylactic reactions, with fatal outcome, have been reported during treatment with CRESEMBA. Symptoms including dyspnea, hypotension, generalized erythema with flushing, and urticaria have been reported in such cases often soon after the initiation of treatment.

Severe Skin Reactions

Severe skin reactions, such as Stevens-Johnson syndrome, have been reported during treatment with other azole antifungal agents.

Discontinue CRESEMBA if a patient develops an anaphylactic or severe cutaneous adverse reaction and initiate supportive treatment as needed. There is no information regarding cross-sensitivity between CRESEMBA and other azole antifungal agents though cross-sensitivity between other triazole agents has been reported. When prescribing CRESEMBA to patients with hypersensitivity to other azoles, monitor for signs and symptoms of hypersensitivity reactions.

5.4 Embryo-Fetal Toxicity

Based on findings from animal reproduction studies, CRESEMBA may cause fetal harm when administered to a pregnant woman. Advise pregnant women of the potential risk to a fetus.

Perinatal mortality was significantly increased in the offspring of pregnant rats dosed orally with isavuconazonium sulfate at 90 mg/kg/day (less than half the maintenance human dose based on AUC comparisons) during pregnancy through the weaning period.

Isavuconazonium chloride administration was associated with dose-related increases in the incidences of rudimentary cervical ribs in rats and rabbits at 30 and 45 mg/kg, respectively, doses equivalent to about 0.2 and 0.1 of the human maintenance dose based on AUC comparisons. In rats, dose-related increases in the incidences of zygomatic arch fusion and supernumerary ribs/rudimentary supernumerary ribs were also noted at 30 mg/kg and above, equivalent to one fifth the maintenance human dose based on AUC comparisons [see Use in Specific Populations (8.1)].

Advise females of reproductive potential to use an effective method of contraception during treatment with CRESEMBA and for 28 days after the final dose [see Use in Specific Populations (8.3)].

5.5 Drug Interactions

Coadministration of CRESEMBA with strong CYP3A4 inhibitors such as ketoconazole or high-dose ritonavir and strong CYP3A4 inducers such as rifampin, carbamazepine, St. John’s wort, or long acting barbiturates is contraindicated [see Contraindications (4) and Drug Interactions (7)].

5.6 Drug Particulates

Following dilution, CRESEMBA intravenous formulation may form precipitate from the insoluble isavuconazole. Administer CRESEMBA through an in-line filter [see Dosage and Administration (2.4)].

6 ADVERSE REACTIONS

The following are discussed in more detail in other sections of the labeling:

- Hepatic Adverse Drug Reactions [see Warnings and Precautions (5.1)]
- Infusion-Related Reactions [see Warnings and Precautions (5.2)]
- Hypersensitivity Reactions [see Warnings and Precautions (5.3)]
- Embryo-Fetal Toxicity [see Warnings and Precautions (5.4)]

6.1 Clinical Trial Experience

Because clinical trials are conducted under widely varying conditions, adverse reaction rates observed in clinical trials of CRESEMBA cannot be directly compared to rates in clinical trials of another drug and may not reflect the rates observed in practice.

Clinical Trials Experience in Adult Patients

A total of 403 adult patients were exposed to CRESEMBA in two clinical trials. The most frequently reported adverse reactions among CRESEMBA-treated patients were nausea (26%), vomiting (25%), diarrhea (22%), headache (17%), elevated liver chemistry tests (16%), hypokalemia (14%), constipation (13%), dyspnea (12%), cough (12%), peripheral edema (11%), and back pain (10%). Serious adverse reactions occurred in 223/403 (55%) of patients and 56/403 (14%) of patients permanently discontinued treatment with CRESEMBA due to an adverse reaction in the two trials. The adverse reactions which most often led to permanent discontinuation of CRESEMBA therapy during the clinical trials were confusional state (0.7%), acute renal failure (0.7%), increased blood bilirubin (0.5%), convulsion (0.5%), dyspnea (0.5%), epilepsy (0.5%), respiratory failure (0.5%), and vomiting (0.5%).

Patients in the clinical trials were immunocompromised with underlying conditions including hematological malignancy, neutropenia post-chemotherapy, graft-versus-host disease, and hematopoietic stem cell transplant. The patient population was 61% male, had a mean age of 51 years (range 17-92, including 85 patients aged greater than 65 years), and was 79% White and 3% Black. One hundred forty-four (144) patients had a duration of CRESEMBA therapy of greater than 12 weeks, with 52 patients receiving CRESEMBA for over six months.

In Trial 1, a randomized, double-blind, active-controlled clinical trial for treatment of invasive aspergillosis, treatment‑emergent adverse reactions occurred in 247/257 (96%), and 255/259 (99%) patients in the CRESEMBA and voriconazole treatment groups, respectively. Adverse reactions resulting in permanent discontinuation were reported in 37 (14%) CRESEMBA-treated patients and 59 (23%) voriconazole-treated patients. Table 3 includes selected adverse reactions which were reported at an incidence of ≥ 5% during CRESEMBA therapy in Trial 1.

In Trial 2, an open-label, non-comparative trial of CRESEMBA in patients with invasive aspergillosis and renal impairment or invasive mucormycosis, adverse reactions occurred in 139/146 (95%) of patients in the CRESEMBA treatment group. Adverse reactions resulting in permanent discontinuation were reported in 19 (13%) CRESEMBA‑treated patients. The frequencies and types of adverse reactions observed in CRESEMBA-treated patients were similar between Trial 1 and Trial 2.

Table 3. Selected Adverse Reactions with Rates of 5% or Greater in CRESEMBA-treated Patients in Trial 1
System Organ Class; Adverse Reactions | Trial 1
System Organ Class; Adverse Reactions | CRESEMBA (N=257) n (%) | Voriconazole (N=259) n (%)
Gastrointestinal disorders
Nausea | 71 (27.6) | 78 (30.1)
Vomiting | 64 (24.9) | 73 (28.2)
Diarrhea | 61 (23.7) | 60 (23.2)
Abdominal pain | 43 (16.7) | 59 (22.8)
Constipation | 36 (14.0) | 54 (20.8)
Dyspepsia | 16 (6.2) | 14 (5.4)
General disorders and administration site conditions
Edema peripheral | 39 (15.2) | 46 (17.8)
Fatigue | 27 (10.5) | 18 (6.9)
Chest pain | 23 (8.9) | 16 (6.2)
Injection site reaction | 16 (6.2) | 4 (1.5)
Hepatobiliary disorders
Elevated liver laboratory tests [Elevated liver laboratory tests include reactions of increased alanine aminotransferase, aspartate aminotransferase, blood alkaline phosphatase, blood bilirubin, and gamma-glutamyl transferase.] | 44 (17.1) | 63 (24.3)
Metabolism and nutrition disorders
Hypokalemia | 49 (19.1) | 58 (22.4)
Decreased appetite | 22 (8.6) | 28 (10.8)
Hypomagnesemia | 14 (5.4) | 27 (10.4)
Musculoskeletal and connective tissue disorders
Back pain | 26 (10.1) | 19 (7.3)
Nervous system disorders
Headache | 43 (16.7) | 38 (14.7)
Psychiatric disorders
Insomnia | 27 (10.5) | 25 (9.7)
Delirium [Delirium includes adverse reactions of agitation, confusional state, delirium, disorientation, and mental status changes.] | 22 (8.6) | 30 (11.6)
Anxiety | 21 (8.2) | 18 (6.9)
Renal and urinary disorders
Renal failure | 26 (10.1) | 21 (8.1)
Respiratory, thoracic and mediastinal disorders
Dyspnea | 44 (17.1) | 35 (13.5)
Acute respiratory failure | 19 (7.4) | 22 (8.5)
Skin and subcutaneous tissue disorders
Rash | 22 (8.6) | 36 (13.9)
Pruritus | 21 (8.2) | 15 (5.8)
Vascular disorders
Hypotension | 21 (8.2) | 28 (10.8)

The following adverse reactions occurred in less than 5% of all CRESEMBA-treated patients in Trial 1 or 2. The list does not include reactions presented in Table 3. This listing includes adverse reactions where a causal relationship to CRESEMBA cannot be ruled out or those which may help the physician in managing the risks to the patients.

- Blood and lymphatic system disorders: agranulocytosis, leukopenia, pancytopenia
- Cardiac disorders: atrial fibrillation, atrial flutter, bradycardia, reduced QT interval on electrocardiogram, palpitations, supraventricular extrasystoles, supraventricular tachycardia, ventricular extrasystoles, cardiac arrest
- Ear and labyrinth disorders: tinnitus, vertigo
- Eye disorders: optic neuropathy
- Gastrointestinal disorders: abdominal distension, gastritis, gingivitis, stomatitis
- General disorders and administration site conditions: catheter thrombosis, malaise, chills
- Hepatobiliary disorders: cholecystitis, cholelithiasis, hepatitis, hepatomegaly, hepatic failure
- Immune system disorders: hypersensitivity
- Injury, poisoning and procedural complications: fall
- Metabolism and nutrition disorders: hypoalbuminemia, hypoglycemia, hyponatremia
- Musculoskeletal and connective tissue disorders: myositis, bone pain, neck pain
- Nervous system disorders: convulsion, dysgeusia, encephalopathy, hypoesthesia, migraine, peripheral neuropathy, paresthesia, somnolence, stupor, syncope, tremor
- Psychiatric disorders: confusion, hallucination, depression
- Renal and urinary disorders: hematuria, proteinuria
- Respiratory, thoracic and mediastinal disorders: bronchospasm, tachypnea
- Skin and subcutaneous tissue disorders: alopecia, dermatitis, exfoliative dermatitis, erythema, petechiae, urticaria
- Vascular disorders: thrombophlebitis

Laboratory Effects
In Trial 1, elevated liver transaminases (alanine aminotransferase or aspartate aminotransferase) greater than three times the upper limit of normal were reported at the end of study treatment in 4.4% of patients who received CRESEMBA. Elevations of liver transaminases greater than ten times the upper limit of normal developed in 1.2% of patients who received CRESEMBA.

Clinical Trials Experience in Pediatric Patients

The clinical safety of CRESEMBA was assessed in 77 pediatric patients who received at least one dose of intravenous or oral CRESEMBA in two uncontrolled studies. Fifteen (19.5%) subjects were in the 1 to < 6 years old cohort, 30 subjects (39.0%) were in the 6 to < 12 years old cohort, and 32 subjects (41.6%) were in the 12 to < 18 years old cohort. The duration of treatment ranged from 1 to 181 days with a median duration of treatment of 15 days. The most frequently reported adverse reactions were diarrhea (26%), abdominal pain (23%), vomiting (21%), elevated liver chemistry tests (18%), rash (14%), nausea (13%), pruritus (13%) and headache (12%). In general, adverse reactions (including serious adverse reactions and adverse reactions leading to permanent discontinuation of CRESEMBA) were similar to those reported in adults.

6.2 Post-Marketing Experience

The following additional adverse reactions have been identified during post-approval use of CRESEMBA. Because these reactions are reported voluntarily from a population of uncertain size, it is not always possible to reliably estimate the frequency or establish a causal relationship to drug exposure.

Immune system disorders: anaphylactic reaction

7 DRUG INTERACTIONS

Isavuconazole is a sensitive substrate of CYP3A4. CYP3A4 inhibitors or inducers may alter the plasma concentrations of isavuconazole.

Isavuconazole is a moderate inhibitor of CYP3A4, and a mild inhibitor of P-glycoprotein (P-gp), and organic cation transporter 2 (OCT2).

Drug interaction studies were conducted to investigate the effect of coadministered drugs on the pharmacokinetics of isavuconazole and the effect of isavuconazole on the pharmacokinetics of coadministered drugs [see Clinical Pharmacology (12.3)].

Table 4. Drug(s) Affecting Pharmacokinetics of CRESEMBA
 | Recommendation | Comments
Ketoconazole | Contraindicate coadministration of all potent CYP3A4 inhibitors | There is more than a 5-fold increase in exposure of isavuconazole upon coadministration with ketoconazole [see Clinical Pharmacology (12.3)].
Lopinavir/ritonavir [400 mg of lopinavir in combination with 100 mg of ritonavir.] | Caution is advised when CRESEMBA is coadministered with lopinavir/ritonavir | There is a 96% increase in exposure of isavuconazole when coadministered with lopinavir/ritonavir [see Clinical Pharmacology (12.3)].
Rifampin | Contraindicate coadministration of all potent CYP3A4 inducers | There is a 97% decrease in exposure of isavuconazole upon coadministration with rifampin [see Clinical Pharmacology (12.3)].

Table 5. The Effect of CRESEMBA on the Pharmacokinetics of Other Drugs
 | Recommendation | Comments
Lopinavir/ritonavir [400 mg of lopinavir in combination with 100 mg of ritonavir.] | Use with Caution | Concomitant administration of lopinavir/ritonavir and CRESEMBA resulted in decreased exposure of lopinavir and ritonavir that could possibly result in loss of antiviral efficacy [see Clinical Pharmacology (12.3)].
Atorvastatin | Use with Caution | Caution should be used when atorvastatin is used with CRESEMBA due to a potential increase in atorvastatin exposure. Monitor patients for adverse reactions that are typical of atorvastatin [see Clinical Pharmacology (12.3)].
Cyclosporine | Use with Caution | Concomitant administration of CRESEMBA and cyclosporine results in increase in cyclosporine exposure. Monitor drug concentrations of cyclosporine and adjust dose as needed [see Clinical Pharmacology (12.3)].
Sirolimus | Use with Caution | Concomitant administration of CRESEMBA and sirolimus results in increase in sirolimus exposure. Monitor drug concentrations of sirolimus and adjust dose as needed [see Clinical Pharmacology (12.3)].
Tacrolimus | Use with Caution | Concomitant administration of CRESEMBA and tacrolimus results in increase in tacrolimus exposure. Monitor drug concentrations of tacrolimus and adjust dose as needed [see Clinical Pharmacology (12.3)].
Midazolam | Use with Caution | Concomitant administration of CRESEMBA and midazolam results in increase in midazolam exposure. Consider dose reduction of midazolam when isavuconazole is coadministered [see Clinical Pharmacology (12.3)].
Bupropion | Use with Caution | Concomitant administration of CRESEMBA and bupropion results in decrease in bupropion exposure. Dose increase of bupropion may be necessary when coadministered with CRESEMBA, but should not exceed the maximum recommended dose [see Clinical Pharmacology (12.3)].
Mycophenolate Mofetil | Use with Caution | Concomitant administration of CRESEMBA and MMF results in increase in MMF exposure. Patients receiving CRESEMBA concurrently with MMF should be monitored for MPA-related toxicities [see Clinical Pharmacology (12.3)].
Digoxin | Use with Caution | Concomitant administration of CRESEMBA and digoxin results in increase in digoxin exposure. Serum digoxin concentrations should be monitored and used for titration when dosed concurrently with CRESEMBA [see Clinical Pharmacology (12.3)].
Vincristine | Avoid Concomitant Use | Avoid concomitant use with CRESEMBA in pediatric and adult patients. CRESEMBA is predicted to have a less than 2‑fold increase in vincristine exposure in pediatric and adult patients [see Clinical Pharmacology (12.3)], which may increase the risk of vincristine-related adverse reactions.

8 USE IN SPECIFIC POPULATIONS

8.1 Pregnancy

Risk Summary

Based on findings from animal studies, CRESEMBA may cause fetal harm when administered to a pregnant woman. There are no available human data on the use of CRESEMBA in pregnant women to evaluate for a drug-associated risk of major birth defects, miscarriage or adverse maternal or fetal outcomes. In animal reproduction studies, perinatal mortality was increased in the offspring of pregnant rats dosed orally with isavuconazonium sulfate at approximately 0.5 times the clinical exposure during pregnancy through the weaning period. In animal studies when isavuconazonium chloride was administered by oral gavage to pregnant rats and rabbits during organogenesis at exposures corresponding to less than the human maintenance dose, increases in the incidences of multiple skeletal abnormalities, including rudimentary cervical ribs and fused zygomatic arches, were observed (see Data). Advise pregnant women of the potential risk to a fetus [see Warnings and Precautions (5.4)].

The estimated background risk of major birth defects and miscarriage for the indicated populations are unknown. All pregnancies have a background risk of birth defect, loss, or other adverse outcomes. In the U.S. general population, the estimated background risk of major birth defects and miscarriage in clinically recognized pregnancies is 2 to 4% and 15 to 20%, respectively.

Data

Animal Data

Isavuconazonium chloride administration during organogenesis (gestational days 6-17 in rats and gestational days 6-18 in rabbits) was associated with dose-related increases in the incidences of rudimentary cervical ribs in rats and rabbits at 30 and 45 mg/kg, respectively, equivalent to about 0.2 and 0.1 times of the clinical exposure based on AUC comparisons. In rats, dose-related increases in the incidences of zygomatic arch fusion and supernumerary ribs/rudimentary supernumerary ribs were also noted at 30 mg/kg and above, equivalent to 0.2 times the human AUC. Skeletal abnormalities have also been observed in embryo-fetal development studies of other azole antifungal agents.

Isavuconazonium sulfate increased perinatal mortality in the pups when orally administered to pregnant rats during pregnancy and lactation (gestational day 6 through postpartum day 20) at doses up to 90 mg/kg/day (approximately 0.5 times the clinical exposure based on AUC comparison). No effect on the duration of pregnancy or delivery was seen in the pups at this same dose.

8.2 Lactation

Risk Summary

There are no data on the presence of isavuconazole in human milk, the effects on the breastfed infant or the effects on milk production. Isavuconazole was present in the milk of lactating rats following intravenous administration. When a drug is present in animal milk, it is likely that the drug will be present in human milk. Therefore, breastfeeding should be discontinued during treatment with CRESEMBA.

8.3 Females and Males of Reproductive Potential

Contraception

CRESEMBA may cause embryo-fetal harm when administered to pregnant women [see Warnings and Precautions (5.4) and Use in Specific Populations (8.1)]. Advise female patients of reproductive potential to use effective contraception during treatment with CRESEMBA and for 28 days after the final dose.

8.4 Pediatric Use

Invasive Aspergillosis

The safety and effectiveness of CRESEMBA for injection for the treatment of invasive aspergillosis have been established in pediatric patients 1 year of age and older. The safety and effectiveness of CRESEMBA capsules for the treatment of invasive aspergillosis have been established in pediatric patients 6 year of age and older weighing 16 kg and greater. Use of CRESEMBA in this age group for treatment of invasive aspergillosis is supported by evidence from one adequate and well-controlled trial in adult patients and additional pharmacokinetic and safety data in pediatric patients 1 year of age and older [see Clinical Pharmacology (12.3)]. Adverse reactions in this pediatric population were similar to those reported in the adult population [see Adverse Reactions (6.1)]. The safety and effectiveness of CRESEMBA capsules for treatment of invasive aspergillosis have not been established in pediatric patients younger than 6 years of age or who weigh less than 16 kg because the oral route of administration was not assessed in this pediatric patient age cohort.

The safety and effectiveness of CRESEMBA for treatment of invasive aspergillosis in pediatric patients less than 1 year of age have not been established.

Invasive Mucormycosis

The safety and effectiveness of CRESEMBA for injection for the treatment of invasive mucormycosis have been established in pediatric patients 1 year of age and older. The safety and effectiveness of CRESEMBA capsules for the treatment of invasive mucormycosis have been established in pediatric patients 6 year of age and older weighing 16 kg and greater. Use of CRESEMBA in this age group for treatment of invasive mucormycosis is supported by one open-label trial in adult patients with invasive mucormycosis, a retrospective review of survival data for adult patients with untreated invasive mucormycosis, and additional pharmacokinetic and safety data in pediatric patients 1 year of age and older [see Clinical Pharmacology (12.3)]. Adverse reactions in this pediatric population were similar to those reported in the adult population [see Adverse Reactions (6.1)]. The safety and effectiveness of CRESEMBA capsules for treatment of invasive mucormycosis have not been established in pediatric patients younger than 6 years of age who weigh less than 16 kg because the oral route of administration was not assessed in this pediatric patient age cohort.

The safety and effectiveness of CRESEMBA for treatment of invasive mucormycosis in pediatric patients less than 1 year of age have not been established.

8.5 Geriatric Use

Of the 547 patients who received CRESEMBA in the Phase 2 and 3 trials, 86 (16%) of patients were greater than 65 years of age and 20 (4%) were greater than 75 years of age. The pharmacokinetics of isavuconazole are comparable in young and elderly subjects (65 years of age and older) [see Clinical Pharmacology (12.3)]. No dose adjustment of CRESEMBA is needed in elderly patients.

No overall differences in safety or effectiveness were observed between these subjects and younger subjects, and other reported clinical experience has not identified differences in responses between the elderly and younger patients, but greater sensitivity of some older individuals cannot be ruled out.

8.6 Renal Impairment

Of the 403 patients who received CRESEMBA in the Phase 3 trials, 79 (20%) of patients had an estimated glomerular filtration rate (GFR) less than 60 mL/min/1.73 m^2. No dose adjustment is needed in patients with mild, moderate, or severe renal impairment, including those patients with End-Stage Renal Disease (ESRD) [see Clinical Pharmacology (12.3)].

8.7 Hepatic Impairment

No dose adjustment is necessary in patients with mild or moderate hepatic impairment (Child-Pugh Class A and B) [see Clinical Pharmacology (12.3)]. CRESEMBA has not been studied in patients with severe hepatic impairment (Child‑Pugh Class C) and should be used in these patients only when the benefits outweigh the risks. Clinical monitoring for CRESEMBA-related adverse reactions is recommended when treating patients with severe hepatic impairment [see Warnings and Precautions (5.1)].

10 OVERDOSAGE

During clinical studies, total daily CRESEMBA doses higher than the recommended dose regimen were associated with an increased rate of adverse reactions. At supratherapeutic doses (three times the recommended maintenance dose) evaluated in a thorough QT study, there were proportionally more treatment-emergent adverse reactions than in the therapeutic dose group (maintenance dose) for the following: headache, dizziness, paresthesia, somnolence, disturbance in attention, dysgeusia, dry mouth, diarrhea, oral hypoesthesia, vomiting, hot flush, anxiety, restlessness, palpitations, tachycardia, photophobia and arthralgia. Adverse reactions leading to discontinuation of study drug occurred in 7 of 39 (17.9%) subjects in the supratherapeutic dose group.

Isavuconazole is not removed by hemodialysis. There is no specific antidote for isavuconazole. Treatment should be supportive with appropriate monitoring.

11 DESCRIPTION

CRESEMBA contains isavuconazonium sulfate, which is the prodrug of isavuconazole, an azole antifungal drug. Isavuconazonium sulfate drug substance is an amorphous, white to yellowish-white powder. The chemical name of isavuconazonium sulfate is glycine, N-methyl-, [2-[[[1-[1-[(2R,3R)-3-[4-(4-cyanophenyl)-2-thiazolyl]-2-(2,5-difluorophenyl)-2-hydroxybutyl]-4H-1,2,4-triazolium-4-yl]ethoxy]carbonyl]methylamino]-3-pyridinyl]methyl ester, sulfate (1:1). The empirical formula is C35H35F2N8O5S·HSO4, the molecular weight is 814.84 and the structural formula is:

CRESEMBA Capsules

CRESEMBA (isavuconazonium sulfate) 74.5 mg capsules are available for oral administration. Each CRESEMBA capsule contains 74.5 mg isavuconazonium sulfate, equivalent to 40 mg isavuconazole. The inactive ingredients include black iron oxide, colloidal silicon dioxide, disodium edetate, gellan gum, hypromellose, magnesium citrate, microcrystalline cellulose, potassium acetate, potassium hydroxide, propylene glycol, purified water, red iron oxide, shellac, sodium lauryl sulfate, stearic acid, strong ammonia solution, talc and titanium dioxide.

CRESEMBA (isavuconazonium sulfate) 186 mg capsules are available for oral administration. Each CRESEMBA capsule contains 186 mg isavuconazonium sulfate, equivalent to 100 mg isavuconazole. The inactive ingredients include black iron oxide, colloidal silicon dioxide, disodium edetate, gellan gum, hypromellose, magnesium citrate, microcrystalline cellulose, potassium acetate, potassium hydroxide, propylene glycol, purified water, red iron oxide, shellac, sodium lauryl sulfate, stearic acid, strong ammonia solution, talc and titanium dioxide.

CRESEMBA for Injection

CRESEMBA (isavuconazonium sulfate) for injection is available for intravenous administration. CRESEMBA for injection is a white to yellow sterile, lyophilized powder containing 372 mg isavuconazonium sulfate, equivalent to 200 mg isavuconazole, per vial. Inactive ingredients included in each vial are 96 mg mannitol and sulfuric acid for pH adjustment.

12 CLINICAL PHARMACOLOGY

12.1 Mechanism of Action

Isavuconazonium sulfate is the prodrug of isavuconazole, an azole antifungal [see Microbiology (12.4)].

12.2 Pharmacodynamics

Pharmacokinetic/Pharmacodynamic Relationship

In patients treated with CRESEMBA for invasive aspergillosis in a controlled trial, there was no significant association between plasma AUC or plasma isavuconazole concentration and efficacy.

Cardiac Electrophysiology

The effect on QTc interval of multiple doses of CRESEMBA capsules was evaluated. CRESEMBA was administered as 2 capsules (equivalent to 200 mg isavuconazole) three times daily on days 1 and 2 followed by either 2 capsules or 6 capsules (equivalent to 600 mg isavuconazole) once daily for 13 days in a randomized, placebo- and active-controlled (moxifloxacin 400 mg single-dose), four-treatment-arm, parallel study in 160 healthy subjects.

Isavuconazole resulted in dose-related shortening of the QTc interval. For the 2-capsule dosing regimen, the least squares mean (LSM) difference from placebo was -13.1 msec at 2 hours postdose [90% CI: -17.1, -9.1 msec]. Increasing the dose to 6 capsules resulted in an LSM difference from placebo of -24.6 msec at 2 hours postdose [90% CI: -28.7, -20.4]. CRESEMBA was not evaluated in combination with other drugs that reduce the QTc interval, so the additive effects are not known.

12.3 Pharmacokinetics

General Pharmacokinetics

In healthy subjects, the pharmacokinetics of isavuconazole following oral administration of CRESEMBA capsules at isavuconazole equivalent doses up to 600 mg per day (6 capsules) are dose proportional (Table 6). Based on a population pharmacokinetics analysis of healthy subjects and patients, the mean plasma half-life of isavuconazole was 130 hours and the mean volume of distribution (Vss) was approximately 450 L following intravenous administration.

Table 6. Steady State Pharmacokinetic Parameters of Isavuconazole Following Administration of 186 mg CRESEMBA Capsules
Parameter | CRESEMBA 186 mg 2 Capsules [Each capsule contains the equivalent of 100 mg of isavuconazole.]; (n = 37) | CRESEMBA 186 mg 6 Capsules; (n = 32)
Cmax (mg/L)
Mean; SD; CV % | 7.5; 1.9; 25.2 | 20.0; 3.6; 17.9
tmax (hr)
Median; Range | 3.0; 2.0 – 4.0 | 4.0; 2.0 – 4.0
AUC (mg•hr/L)
Mean; SD; CV % | 121.4; 35.8; 29.5 | 352.8; 72.0; 20.4

Following oral administration of CRESEMBA capsules at an isavuconazole equivalent dose of 200 mg in 66 fasted healthy male subjects, a single dose administration of two 186 mg CRESEMBA capsules and five 74.5 mg CRESEMBA capsules exhibited a mean (SD) Cmax and AUC of 3.3 (0.6) mg/L and 112.2 (30.3) mg·hr/L, respectively, and 3.3 (0.6) mg/L and 118.0 (33.1) mg·hr/L, respectively.

Absorption

After oral administration of CRESEMBA in healthy volunteers, the active moiety, isavuconazole, generally reaches maximum plasma concentrations (Cmax) 2 hours to 3 hours after single and multiple dosing. The absolute bioavailability of isavuconazole following oral administration of CRESEMBA is 98%. No significant concentrations of the prodrug or inactive cleavage product were seen in plasma after oral administration.

Following intravenous administration of CRESEMBA, maximal plasma concentrations of the prodrug and inactive cleavage product were detectable during infusion and declined rapidly following the end of administration. The prodrug was below the level of detection by 1.25 hours after the start of a one-hour infusion. The total exposure of the prodrug based on AUC was less than 1% that of isavuconazole. The inactive cleavage product was quantifiable in some subjects up to 8 hours after the start of infusion. The total exposure of inactive cleavage product based on AUC was approximately 1.3% that of isavuconazole.

CRESEMBA given orally as an intravenous solution administered via nasogastric (NG) tube provides systemic isavuconazole exposure that is similar to the oral capsule (Table 7).

Table 7. Statistical Comparison of Plasma Pharmacokinetics of Isavuconazole Following Single Oral Dose Administration of 2 Capsules of 186 mg (Equivalent to 200 mg Isavuconazole) and Single Intravenous Solution Dose Administration of 372 mg (Equivalent to 200 mg Isavuconazole) via Nasogastric (NG) Tube in Healthy Adult Subjects Under Fasted Conditions
 | CRESEMBA IV Solution via NG Tube |  | CRESEMBA Oral Capsules |  | NG Tube/Oral Capsule
Pharmacokinetic Parameter | N | Mean (%CV) | N | Mean (%CV) | GMR (90% CI)
Cmax (mg/L) | 13 | 2.3 (23.6) | 13 | 2.2 (26.7) | 105.34 (89-124)
AUC0-72hr; (mg·hr/L) | 13 | 34.9 (22.1) | 13 | 35.8 (24.6) | 97.81 (93-103)
AUC0-∞; (mg·hr/L) | 12 | 98.1 (44.5) | 12 | 100.1 (46.8) | 99.27 (93-106)
GMR = Geometric least-squares mean ratio; CI = confidence interval

Effect of Food

Coadministration of CRESEMBA equivalent to isavuconazole 400 mg oral dose with a high-fat meal reduced isavuconazole Cmax by 9% and increased AUC by 9%. CRESEMBA can be taken with or without food.

Distribution

Isavuconazole is extensively distributed with a mean steady state volume of distribution (Vss) of approximately 450 L. Isavuconazole is highly protein bound (greater than 99%), predominantly to albumin.

Elimination

Metabolism

In in vitro studies isavuconazonium sulfate is rapidly hydrolyzed in blood to isavuconazole by esterases, predominantly by butylcholinesterase. Isavuconazole is a substrate of cytochrome P450 enzymes 3A4 and 3A5.

Following single doses of [cyano ^14C] isavuconazonium and [pyridinylmethyl ^14C] isavuconazonium in humans, in addition to the active moiety (isavuconazole) and the inactive cleavage product, a number of minor metabolites were identified. Except for the active moiety isavuconazole, no individual metabolite was observed with an AUC greater than 10% of drug-related material.

In vivo studies indicate that CYP3A4, CYP3A5 and subsequently uridine diphosphate-glucuronosyltransferases (UGT) are involved in the metabolism of isavuconazole.

Excretion

Following oral administration of radio-labeled isavuconazonium sulfate to healthy volunteers, a mean of 46.1% of the total radioactive dose was recovered in the feces and 45.5% was recovered in the urine.

Renal excretion of isavuconazole itself was less than 1% of the dose administered.

The inactive cleavage product is primarily eliminated by metabolism and subsequent renal excretion of the metabolites. Renal elimination of intact cleavage product was less than 1% of the total dose administered. Following intravenous administration of radio-labeled cleavage product, 95% of the total radioactive dose was excreted in the urine.

Special populations

Geriatric Patients

The AUC of isavuconazole following a single oral dose of CRESEMBA equivalent to 200 mg isavuconazole in elderly subjects (65 years and older) was similar to that in younger volunteers (18 years to 45 years). The AUC was similar between younger female and male subjects and between elderly and younger males.

Elderly female AUC estimates were 38% and 47% greater than AUC estimates obtained in elderly males and younger females, respectively. The pharmacokinetic difference in elderly females receiving CRESEMBA are not considered to be clinically significant. Therefore, no dose adjustment is required based on age and gender.

Pediatric Patients

The pharmacokinetics of isavuconazole were evaluated in two clinical studies (N = 73) in pediatric patients aged 1 to less than 18 years of age which included twenty-eight patients with at least possible invasive aspergillosis or possible invasive mucormycosis.

Table 8. Derived Steady State Isavuconazole AUC (mg•hr/L) values in Pediatric Patients, by Age Group
Dosage | 15 mg/kg [Estimated AUCss values of 15 mg/kg that were derived from existing values of pediatric patients that received 10 mg/kg of CRESEMBA for injection administered intravenously.] | 10 mg/kg [CRESEMBA for injection administered intravenously.] | 10 mg/kg; or; Maximum Dose of 372 mg [CRESEMBA for injection administered intravenously or CRESEMBA capsules administered orally.]
Age Group | 1 to < 3 years; (n=5) | 3 to < 6 years; (n=10) | 6 to < 12 years; (n=29) | 12 to < 18 years; (n=29)
Mean | 80.2 | 103.3 | 97.3 | 104.2
Median | 64.3 | 110.3 | 87.7 | 97.7
Minimum - Maximum | 53.7 - 155 | 51.5 – 159.1 | 37.8– 153.8 | 35.5 – 215.6

Race

A 2-compartment population pharmacokinetic model was developed to assess the pharmacokinetics of isavuconazole between healthy Western and Chinese subjects. Chinese subjects were found to have on average a 40% lower clearance compared to Western subjects (1.6 L/hr for Chinese subjects as compared to 2.6 L/hr for Western subjects) and therefore approximately 50% higher AUC than Western subjects. Body mass index (BMI) did not play a role in the observed differences. No dose adjustment is recommended for Chinese patients.

Gender

AUC estimates were similar between young female and male subjects (18 years to 45 years). There was a difference in AUC for elderly females (see Geriatric section above). No dose adjustment is required based on gender.

Patients with Renal Impairment

Total isavuconazole AUC and Cmax were not affected to a clinically meaningful extent in subjects with mild, moderate and severe renal impairment relative to healthy controls. No dose adjustment is necessary in patients with renal impairment.

Isavuconazole is not readily dialyzable. A dose adjustment is not warranted in patients with ESRD.

Patients with Hepatic Impairment

After a single-dose of CRESEMBA equivalent to 100 mg of isavuconazole was administered to 32 patients with mild (Child-Pugh Class A) hepatic impairment and 32 patients with moderate (Child-Pugh Class B) hepatic impairment (16 intravenous and 16 oral patients per Child-Pugh Class), the least squares mean systemic exposure (AUC) increased 64% and 84% in the Child-Pugh Class A group and the Child-Pugh Class B group, respectively, relative to 32 age and weight-matched healthy subjects with normal hepatic function. Mean Cmax was 2% lower in the Child-Pugh Class A group and 30% lower in the Child-Pugh Class B group. The population pharmacokinetic evaluation of isavuconazole in healthy subjects and patients with mild and moderate hepatic impairment demonstrated that the mild and moderate hepatic impairment population had 40% and 48% lower isavuconazole clearance (CL) values, respectively, compared to the healthy population. It is recommended that the standard CRESEMBA loading dose and maintenance dose regimen be utilized in patients with mild to moderate hepatic disease. CRESEMBA has not been studied in patients with severe hepatic impairment (Child-Pugh Class C).

Drug Interaction Studies

In Vitro Studies

CYP450 Enzymes: Isavuconazole is a substrate of CYP3A4 and CYP3A5. Isavuconazole is an inhibitor of CYP3A4, CYP2C8, CYP2C9, CYP2C19, and CYP2D6. Isavuconazole is an inducer of CYP3A4, CYP2B6, CYP2C8, and CYP2C9.

Transporter Systems: Isavuconazole is an inhibitor of P-gp-, BCRP- and OCT2.

Clinical Studies and Model-Informed Approaches

The effect of coadministration of drugs on the pharmacokinetics of isavuconazole and the effect of isavuconazole on the pharmacokinetics of coadministered drugs were studied after single and multiple doses of isavuconazole in healthy subjects.

The effects of ketoconazole, rifampin, lopinavir/ritonavir, and esomeprazole on isavuconazole are shown in Figure 1.

Ketoconazole: As a strong CYP3A4 inhibitor, ketoconazole increased the isavuconazole Cmax by 9% and isavuconazole AUC by 422% after multiple-dose administration of ketoconazole (200 mg twice daily) for 24 days and a single-dose of CRESEMBA equivalent to 200 mg of isavuconazole. Isavuconazole is a sensitive CYP3A4 substrate and use with strong CYP3A4 inhibitors are contraindicated per Section 4 and Figure 1.

Lopinavir/Ritonavir: Lopinavir/ritonavir (400 mg/100 mg twice daily) increased the Cmax and AUC of isavuconazole by 74% and 96%, respectively, with concurrent decreases in the mean AUCs of lopinavir and ritonavir by 27% and 31%, respectively.

Rifampin: Rifampin (600 mg) decreased the mean Cmax and AUC of isavuconazole by 75% and 97%, respectively, when coadministered with multiple doses of CRESEMBA and thus, coadministration of CRESEMBA with strong CYP3A4 inducers is contraindicated.

Figure 1. The Effect of Coadministered Drugs on Isavuconazole Exposure

The effects of isavuconazole on ritonavir, lopinavir, prednisone, combined oral contraceptives (ethinyl estradiol and norethindrone), cyclosporine, atorvastatin, sirolimus, midazolam, and tacrolimus are shown in Figure 2.

CYP3A4 Substrates: CRESEMBA increased the systemic exposure of sensitive CYP3A4 substrates midazolam, sirolimus and tacrolimus approximately 2-fold, and therefore CRESEMBA is a moderate inhibitor of CYP3A4.

Figure 2. The Effect of Isavuconazole on Coadministered CYP3A4 Substrate Medications

The effects of isavuconazole on other CYP substrates: caffeine, bupropion, methadone, repaglinide, warfarin, omeprazole, and dextromethorphan, are shown in Figure 3.

Figure 3. The Effect of Isavuconazole on Exposure of Coadministered CYP Substrate Medications

The effects of isavuconazole on the substrates of UGT and transporters: mycophenolate mofetil (MMF), methotrexate, metformin, and digoxin are shown in Figure 4.

Figure 4. The Effect of Isavuconazole on Exposure on the Substrates of UGT and Transporters

Vincristine: Vincristine (P-gp substrate) exposure is predicted to increase by less than 2-fold in pediatric and adult patients following concomitant administration with CRESEMBA.

12.4 Microbiology

Mechanism of Action

Isavuconazonium sulfate is the prodrug of isavuconazole, an azole antifungal drug. Isavuconazole inhibits the synthesis of ergosterol, a key component of the fungal cell membrane, through the inhibition of cytochrome P-450 dependent enzyme lanosterol 14-alpha-demethylase. This enzyme is responsible for the conversion of lanosterol to ergosterol. An accumulation of methylated sterol precursors and a depletion of ergosterol within the fungal cell membrane weakens the membrane structure and function. Mammalian cell demethylation is less sensitive to isavuconazole inhibition.

Resistance

There is a potential for development of resistance to isavuconazole.

The mechanism of resistance to isavuconazole, like other azole antifungals, is likely due to multiple mechanisms that include substitutions in the target gene CYP51. Changes in sterol profile and elevated efflux pump activity were observed; however, the clinical relevance of these findings is unclear.

In vitro and animal studies suggest cross-resistance between isavuconazole and other azoles. The relevance of cross‑resistance to clinical outcome has not been fully characterized; however, patients failing prior azole therapy may require alternative antifungal therapy.

Antimicrobial Activity

Isavuconazole has activity against most strains of the following microorganisms, both in vitro and in clinical infections: Aspergillus flavus, Aspergillus fumigatus, Aspergillus niger, and Mucorales such as Rhizopus oryzae and Mucormycetes species [see Clinical Studies (14)].

Susceptibility Testing

For specific information regarding susceptibility test interpretive criteria and associated test methods and quality control standards recognized by FDA for this drug, please see: https://www.fda.gov/STIC.

13 NONCLINICAL TOXICOLOGY

13.1 Carcinogenesis, Mutagenesis, Impairment of Fertility

Carcinogenesis

In a 2-year rat carcinogenicity study and a 2-year mouse carcinogenicity study, dose-related increases in hepatocellular adenomas and/or carcinomas were observed in male and female B6C3F1/Crl mice, and male, but not female Han Wistar rats at doses as low as 0.1 times the exposure seen in humans administered the maintenance dose. Hepatic hemangiomas were increased in female mice at 300 mg/kg, at an exposure similar to the maintenance dose. Hepatoblastoma were increased in male mice at 100 mg/kg, about 0.4 times the systemic exposures based on AUC comparisons.

Thyroid follicular cell adenomas were observed in male and female rats at doses as low as 60 mg/kg in male rats (about 0.2 times the human clinical maintenance dose). The relevance of the rat thyroid tumors to human carcinogenic risk remains unclear.

A significant increase in the incidence of skin fibromas was seen in male rats at 300 mg/kg, exposures 0.8 times the human exposure at the human clinical maintenance dose. Uterine adenocarcinomas were observed in female rats at 200 mg/kg, at systemic exposures similar to the human exposure at the human clinical maintenance dose.

Mutagenesis

No mutagenic or clastogenic effects were detected in the in vitro bacterial reverse mutation assay and the in vivo bone marrow micronucleus assay in rats.

Impairment of Fertility

Oral administration of isavuconazonium sulfate did not affect the fertility in male or female rats treated at doses up to 90 mg/kg/day (approximately 0.3 times the systemic exposure at the human clinical maintenance dose).

14 CLINICAL STUDIES

14.1 Treatment of Invasive Aspergillosis

Trial 1 was a randomized, double-blind, non-inferiority active controlled trial which evaluated the safety and efficacy of CRESEMBA versus voriconazole for primary treatment of invasive fungal disease caused by Aspergillus species or other filamentous fungi. Eligible patients had proven, probable, or possible invasive fungal infections per European Organisation for Research and Treatment of Cancer/Mycoses Study Group (EORTC/MSG) criteria^1. Patients were stratified by history of allogeneic bone marrow transplant, uncontrolled malignancy at baseline, and by geographic region. The mean age of patients was 51 years (range 17-87) and the majority were Caucasians (78%), male (60%), with fungal disease involving the lungs (95%). At least one Aspergillus species was identified in 30% of the subjects; A. fumigatus and A. flavus were the most common pathogens identified. There were few patients with other Aspergillus species:
A. niger, A. sydowii, A. terreus, and A. westerdijkiae. Baseline risk factors are presented in Table 9.

Table 9. Baseline Risk Factors in Intent-To-Treat (ITT [ITT includes all randomized patients who received at least one dose of study drug.]) Population
 | CRESEMBA N=258 n (%) | Voriconazole N=258 n (%)
Hematologic Malignancy | 211 (82) | 222 (86)
Allogeneic Hematopoietic Stem Cell Transplant | 54 (21) | 51 (20)
Neutropenia [Neutropenia defined as less than 500 cells/mm^3.] | 163 (63) | 175 (68)
Corticosteroid Use | 48 (19) | 39 (15)
T-Cell Immunosuppressant Use | 111 (43) | 109 (42)

Patients randomized to receive CRESEMBA treatment were administered a loading dose intravenously of 372 mg of isavuconazonium sulfate (equivalent to 200 mg of isavuconazole) every 8 hours for the first 48 hours. Beginning on Day 3, patients received intravenous or oral therapy of 372 mg of isavuconazonium sulfate (equivalent to 200 mg of isavuconazole) once daily. Patients randomized to receive voriconazole treatment were administered voriconazole intravenously with a loading dose of 6 mg/kg every 12 hours for the first 24 hours followed by 4 mg/kg intravenously every 12 hours for the following 24 hours. Therapy could then be switched to an oral formulation of voriconazole at a dose of 200 mg every 12 hours. In this trial, the protocol-defined maximum treatment duration was 84 days. Mean treatment duration was 47 days for both treatment groups, of which 8 to 9 days was by an intravenous route of administration.

All-cause mortality through Day 42 in the overall population (ITT) was 18.6% in the CRESEMBA treatment group and 20.2% in the voriconazole treatment group for an adjusted treatment difference of -1.0% with 95% confidence interval of -8.0% to 5.9%. Similar results were seen in patients with proven or probable invasive aspergillosis confirmed by serology, culture or histology (see Table 10).

Table 10. All-Cause Mortality Through Day 42
 | CRESEMBA |  | Voriconazole
 | N | All-cause Mortality n (%) | N | All-cause Mortality n (%) | Difference [Adjusted treatment difference (CRESEMBA-voriconazole) by Cochran-Mantel-Haenszel method stratified by the randomization factors.] (95% CI)%
ITT | 258 | 48 (18.6) | 258 | 52 (20.2) | -1.0 (-8.0, 5.9)
Proven or Probable Invasive Aspergillosis | 123 | 23 (18.7) | 108 | 24 (22.2) | -2.7 (-13.6, 8.2)

Overall success at End-of-Treatment (EOT) was assessed by a blinded, independent Data Review Committee (DRC) using pre-specified clinical, mycological, and radiological criteria. In the subgroup of patients with proven or probable invasive aspergillosis confirmed by serology, culture or histology, overall success at EOT was seen in 35% of CRESEMBA-treated patients compared to 38.9% of voriconazole-treated patients (see Table 11).

Table 11. Overall Response Success at End-of-Treatment
 | CRESEMBA |  | Voriconazole
 | N | Success n (%) | N | Success n (%) | Difference [Adjusted treatment difference (CRESEMBA-voriconazole) by Cochran-Mantel-Haenszel method stratified by the randomization factors.] (95% CI)%
Proven or Probable Invasive Aspergillosis | 123 | 43 (35.0) | 108 | 42 (38.9) | -4.0 (-16.3, 8.4)

14.2 Treatment of Invasive Mucormycosis

Trial 2, an open-label, non-comparative trial, evaluated the safety and efficacy of a subset of patients with invasive mucormycosis. Thirty-seven (37) patients had proven or probable mucormycosis according to criteria based on those established by the European Organisation for Research and Treatment of Cancer/Mycoses Study Group^1. Rhizopus oryzae and Mucormycetes were the most common pathogens identified. There were few patients with other Mucorales: Lichtheimia corymbifera, Mucor amphibiorum, Mucor circinelloides, Rhizomucor pusillus, Rhizopus azygosporus, and Rhizopus microsporus. The patients were white (68%), male (81%), and had a mean age of 49 years (range 22-79). Fifty-nine percent (59%) of patients had pulmonary disease involvement, half of whom also had other organ involvement. The most common non-pulmonary disease locations were sinus (43%), eye (19%), CNS (16%) and bone (14%). Baseline risk factors are presented in Table 12. The Independent Data Review Committee classified patients receiving CRESEMBA as primary therapy, or for invasive mold disease refractory to, or patients intolerant of other antifungal therapy.

Table 12. Baseline Risk Factors in Mucorales Patients
 | Primary N=21 n (%) | Refractory N=11 n (%) | Intolerant N=5 n (%) | Total N=37 n (%)
Hematologic Malignancy | 11 (52) | 7 (64) | 4 (80) | 22 (60)
Allogeneic Hematopoietic Stem Cell Transplant | 4 (19) | 4 (36) | 5 (100) | 13 (35)
Neutropenia [Neutropenia is defined as less than 500 cells/mm^3.] | 4 (19) | 5 (46) | 1 (20) | 10 (27)
Corticosteroid Use | 5 (24) | 3 (27) | 2 (40) | 10 (27)
T-Cell Immunosuppressant Use | 7 (33) | 6 (55) | 5 (100) | 18 (49)
Diabetic | 4 (19) | 0 | 0 | 4 (11)
Therapy status assessed by the Independent Data Review Committee: Primary = patients received CRESEMBA as primary treatment; refractory = patient’s underlying infection not adequately treated by prior therapy; intolerant = patients unable to tolerate prior therapy.

Patients were treated with CRESEMBA intravenously or via oral administration at the recommended doses. Median treatment duration was 102 days for patients classified as primary, 33 days for refractory, and 85 days for intolerant [see Dosage and Administration (2.2)].

For patients with invasive mucormycosis, all-cause mortality through Day 42 and success in overall response at the End‑of-Treatment as assessed by the Independent Data Review Committee is shown in Table 13. These results provide evidence that CRESEMBA is effective for the treatment of mucormycosis, in light of the natural history of untreated mucormycosis. However, the efficacy of CRESEMBA for the treatment of invasive mucormycosis has not been evaluated in concurrent, controlled clinical trials.

Table 13. All-Cause Mortality and Overall Response Success in Mucorales Patients
 | Primary N=21 | Refractory N=11 | Intolerant N=5 | Total N=37
All-cause Mortality Through Day 42 | 7 (33%) | 5 (46%) | 2 (40%) | 14 (38%)
Overall Response Success Rate at End-of-Treatment | 6/19 [Two primary mucormycosis patients were not assessed at End-of-Treatment due to ongoing treatment.] (32%) | 4/11 (36%) | 1/5 (20%) | 11/35 (31%)

15 REFERENCES

1. DePauw, B., Walsh, T.J., Donnelly, J.P., et al. (2008) Revised Definitions of Invasive Fungal Disease from the European Organization for Research and Treatment of Cancer Invasive Fungal Infections Quadrature Group and National Institute of Allergy and Infectious Diseases Mycoses Study Group (EORTC/MSG) consensus group. Clinical Infectious Diseases 46:1813-1821.

16 HOW SUPPLIED/STORAGE AND HANDLING

16.1 How Supplied

CRESEMBA Capsules
CRESEMBA (isavuconazonium sulfate) 74.5 mg capsules are supplied as opaque capsules and have a Swedish orange (reddish-brown) body imprinted with the Astellas logo in black ink and a Swedish orange cap imprinted with “557” in black ink. Each capsule contains 74.5 mg isavuconazonium sulfate (equivalent to 40 mg of isavuconazole) and is packaged as follows:

35-count carton (contains seven individual aluminum child-resistant blister packs of 5 capsules per sheet with desiccant) | NDC 0469-2860-35

CRESEMBA (isavuconazonium sulfate) 186 mg capsules are supplied as opaque and elongated capsules and have a Swedish orange (reddish-brown) body imprinted with the Astellas logo in black ink and a white cap imprinted with “766” in black ink. Each capsule contains 186 mg isavuconazonium sulfate (equivalent to 100 mg of isavuconazole) and is packaged as follows:

14-count carton (contains two individual aluminum child-resistant blister packs of 7 capsules per sheet with desiccant) | NDC 0469-0520-02

CRESEMBA for Injection
CRESEMBA (isavuconazonium sulfate) for injection is supplied as white to yellow sterile lyophilized powder containing 372 mg isavuconazonium sulfate (equivalent to 200 mg isavuconazole) in a single-dose vial and is packaged as follows:

Individually packaged single-dose vial | NDC 0469-0420-01

16.2 Storage and Handling

CRESEMBA Capsules

Store CRESEMBA capsules at 20°C to 25°C (68°F to 77°F) in the original packaging to protect from moisture. Excursions are permitted from 15°C to 30°C (59°F to 86°F) [See USP Controlled Room Temperature].

CRESEMBA for Injection

Store CRESEMBA for injection unreconstituted vials at 2°C to 8°C (36°F to 46°F) in a refrigerator. CRESEMBA for injection is a single-dose vial of unpreserved sterile lyophile.

Following reconstitution of the lyophile with water for injection USP, the reconstituted solution should be used immediately, or stored between 5°C to 25°C (41°F to 77°F) for a maximum of 1 hour prior to preparation of the patient infusion solution [see Dosage and Administration (2.4)]. The prepared infusion solution should be kept for not more than 6 hours at room temperature [20°C to 25°C (68°F to 77°F)] or 24 hours at 2°C to 8°C (36°F to 46°F) prior to use [see Dosage and Administration (2.5)]. For nasogastric tube use, the reconstituted solution should be stored between 5°C to 25°C (41°F to 77°F) and used within 1 hour of reconstitution [see Dosage and Administration (2.6)].

17 PATIENT COUNSELING INFORMATION

Advise the patient to read the FDA-approved patient labeling (Patient Information).

Important Administration Instructions

Advise patients that CRESEMBA can be taken with or without food. Each capsule should be swallowed whole. Do not chew, crush, dissolve, or open the capsules [see Dosage and Administration 2.1].

Drug Interactions

Advise patients to inform their physician if they are taking other drugs or before they begin taking other drugs as certain drugs can decrease or increase the plasma concentrations of CRESEMBA [see Warnings and Precautions (5.5)].

CRESEMBA can decrease or increase the plasma concentrations of other drugs [see Drug Interactions (7)].

Pregnancy

Advise patients to inform their physician if they are pregnant, plan to become pregnant, or are nursing [see Warnings and Precautions (5.4) and Pregnancy (8.1)].

Allergic Reactions

Advise patients to inform their physician immediately if they have ever had an allergic reaction to isavuconazole or other antifungal medicines such as ketoconazole, fluconazole, itraconazole, posaconazole, or voriconazole. Advise patients to discontinue CRESEMBA and seek immediate medical attention if any signs or symptoms of severe allergic reaction occur [see Warnings and Precautions (5.3)].
Marketed and Distributed by:
Astellas Pharma US, Inc.
Northbrook, IL 60062
CRESEMBA is a registered trademark of Astellas US LLC.

Licensed from: Basilea Pharmaceutica International Ltd.
02625-ISA-USA

Patient Information

CRESEMBA® (Crē sem’ bah)

(isavuconazonium sulfate)

capsules, for oral use
CRESEMBA® (Crē sem’ bah)

(isavuconazonium sulfate)

for injection, for intravenous use

Read this Patient Information before you or your child start taking CRESEMBA and each time you or your child get a refill. There may be new information. This information does not take the place of talking with your or your child’s healthcare provider about your medical condition or your treatment.

What is CRESEMBA?

CRESEMBA is a prescription medicine used to treat certain types of fungal infections in the blood or body called invasive aspergillosis and invasive mucormycosis as follows:

- CRESEMBA for injection: adults and children 1 year of age and older
- CRESEMBA capsules: adults and children 6 years of age and older who weigh 35 pounds (16 kg) or more

It is not known if CRESEMBA capsules are safe and effective in children younger than 6 years of age or who are 6 years of age and older but weigh less than 35 pounds (16 kg).

It is not known if CRESEMBA is safe and effective in children under 1 year of age.

Who should not take CRESEMBA?
Do not take CRESEMBA if you or your child:

- are allergic to CRESEMBA or any of the ingredients. See the end of this Patient Information leaflet for a complete list of ingredients in CRESEMBA.
- are taking any of the following medicines:

- ketoconazole
- high-dose ritonavir

- rifampin
- carbamazepine

- St. John’s wort (herbal supplement)
- long-acting barbiturates

- have a genetic problem that affects the electrical system of the heart (familial short QT syndrome).

Talk to your or your child’s healthcare provider or pharmacist if you are not sure if you are taking any of these medicines or have any of the conditions listed above.

Do not start taking new medicines without talking to your or your child’s healthcare provider or pharmacist.

Before you or your child take CRESEMBA, tell your healthcare provider about all of your medical conditions, including if you or your child:

- have or ever had an abnormal heart rate or rhythm. Your healthcare provider may order a test to check your heart (ECG) before starting CRESEMBA.
- have liver problems. Your healthcare provider may do blood tests to make sure you can take CRESEMBA.
- have ever had an allergic reaction to other antifungal medicines such as ketoconazole, fluconazole, itraconazole, voriconazole or posaconazole.
- are pregnant or plan to become pregnant. CRESEMBA may harm your unborn baby. Talk to your healthcare provider if you are pregnant or plan to become pregnant. Women who can become pregnant should use effective birth control while taking CRESEMBA and for 28 days after the last CRESEMBA dose. Talk to your healthcare provider about birth control methods that may be right for you.
- are breastfeeding or plan to breastfeed. CRESEMBA can pass into your breast milk and may harm your baby. Talk to your healthcare provider about the best way to feed your baby if you take CRESEMBA.

Tell your healthcare provider about all the medicines you or your child take, including prescription and over-the-counter medicines, vitamins, and herbal supplements.

CRESEMBA may affect the way other medicines work, and other medicines may affect how CRESEMBA works and can cause side effects.

Ask your or your child’s healthcare provider or pharmacist for a list of these medicines if you are not sure.

Know the medicines you or your child take. Keep a list of them with you to show your or your child’s healthcare provider and pharmacist when you get a new medicine.

How should I take CRESEMBA?

- Take CRESEMBA exactly as your or your child’s healthcare provider tells you to take it.
- Do not stop taking CRESEMBA until your or your child’s healthcare provider tells you to.
- If you or your child take too much CRESEMBA, call your healthcare provider or go to the nearest hospital emergency room right away.
- CRESEMBA capsules can be taken with or without food.
- Swallow CRESEMBA capsules whole. Do not chew, crush, dissolve, or open the capsules.
- CRESEMBA for injection can be given through a nasogastric tube by your or your child’s healthcare provider.
- Do not give CRESEMBA capsules through a nasogastric tube.

Instructions on opening CRESEMBA capsules blister packaging:

CRESEMBA capsules are in child-resistant blister packaging.

Each blister section contains two pockets: one pocket for the CRESEMBA capsule and one pocket for the desiccant to protect the capsule from moisture (located to the left of the capsule).

- Only open the blister packaging at time of use. Make sure only the CRESEMBA capsule pocket is opened.
- Do not puncture the pocket containing the desiccant.
- Do not swallow or use the desiccant.

What are the possible side effects of CRESEMBA?

CRESEMBA may cause serious side effects, including:

- liver problems. Liver problems can happen in some people taking CRESEMBA. Some people who also have other serious medical problems may get severe liver problems which can lead to hepatitis, gallbladder problems, liver failure or death. Your or your child’s healthcare provider should do blood tests to check your liver before you start and while you are taking CRESEMBA. Call your or your child’s healthcare provider right away if you have any of the following symptoms of liver problems:

- itchy skin
- nausea or vomiting

- yellowing of your eyes
- feeling very tired

- flu-like symptoms

- infusion reactions. Infusion reactions can happen in people receiving CRESEMBA intravenously. If an infusion reaction happens, your or your child’s infusion will be stopped. Symptoms of an infusion reaction may include:

- low blood pressure
- difficulty breathing

- chills
- dizziness

- numbness and tingling
- changes in your sense of touch (hypoesthesia)

- severe allergic reactions. Severe allergic reactions including death can happen in some people taking CRESEMBA. Symptoms of a severe allergic reaction may include:

- swelling of your face, lips, mouth, or tongue
- wheezing
- skin rash redness, or swelling
- fast heartbeat or pounding in your chest

- trouble breathing
- severe itching
- dizziness or fainting
- sweating

Stop taking CRESEMBA and call your or your child’s healthcare provider or go to the nearest hospital emergency room right away if you have any of the symptoms listed above.

- drug interactions with cyclosporine, sirolimus, or tacrolimus. If you or your child take CRESEMBA with cyclosporine, sirolimus, or tacrolimus, your blood levels of cyclosporine, sirolimus, or tacrolimus may increase. Serious side effects can happen in your or your child’s kidney or brain if you have high levels of cyclosporine, sirolimus, or tacrolimus in your blood. Your or your child’s healthcare provider should do blood tests to check your levels of cyclosporine, sirolimus, or tacrolimus if you are taking these medicines while taking CRESEMBA. Tell your or your child’s healthcare provider right away if you have swelling in your arm or leg or shortness of breath.
- medicine interactions. Taking CRESEMBA with some other medicines may affect the way other medicines work causing serious side effects. Other medicines may affect the way CRESEMBA works, causing serious side effects. Tell your or your child’s healthcare provider about all the medicines you take.

The most common side effects of CRESEMBA in adults include:

- nausea
- vomiting
- diarrhea
- headache

- changes in the level of a liver enzyme in your blood
- low potassium
- constipation
- shortness of breath

- cough
- swelling of arms or legs
- back pain

The most common side effects of CRESEMBA in children include:

- diarrhea
- stomach pain
- vomiting
- changes to the level of a liver enzyme in your blood

- rash
- nausea
- itching
- headache

Tell your or your child’s healthcare provider if you have any side effect that bothers you or that does not go away.

These are not all the possible side effects of CRESEMBA. For more information, ask your or your child’s healthcare provider or pharmacist.

Call your doctor for medical advice about side effects. You may report side effects to FDA at 1-800-FDA-1088.

How should I store CRESEMBA capsules?

- Store CRESEMBA at room temperature between 68°F to 77°F (20°C to 25°C).
- Keep CRESEMBA in the original package and protect it from moisture.
- Do not remove CRESEMBA from its original packaging.
- Safely throw away medicine that is out of date or no longer needed.

Keep CRESEMBA and all medicines out of the reach of children.

General information about the safe and effective use of CRESEMBA.

Medicines are sometimes prescribed for purposes other than those listed in a Patient Information leaflet. Do not use CRESEMBA for a condition for which it was not prescribed. Do not give CRESEMBA to other people, even if they have the same symptoms that you have. It may harm them.

This Patient Information leaflet summarizes the most important information about CRESEMBA. If you would like more information, talk with your healthcare provider. You can ask your healthcare provider or pharmacist for information about CRESEMBA that is written for health professionals.

What are the ingredients of CRESEMBA capsules?

Active ingredient: isavuconazonium sulfate.

Inactive ingredients: black iron oxide, colloidal silicon dioxide, disodium edetate, gellan gum, hypromellose, magnesium citrate, microcrystalline cellulose, potassium acetate, potassium hydroxide, propylene glycol, purified water, red iron oxide, shellac, sodium lauryl sulfate, stearic acid, strong ammonia solution, talc and titanium dioxide.

Marketed and Distributed by:

Astellas Pharma US, Inc. Northbrook, IL 60062

390714-ISA- USA

CRESEMBA is a registered trademark of Astellas US LLC.

Licensed from: Basilea Pharmaceutica International Ltd.

For more information go to www.CRESEMBA.com or call 1-800-727-7003.

This Patient Information has been approved by the U.S. Food and Drug Administration.

Revised: 12/2023

Package/Label Display Panel – CRESEMBA capsules 186 mg – blister carton label

NDC 0469-0520-02

CRESEMBA®
(isavuconazonium sulfate) capsules

186 mg*

*equivalent to 100 mg isavuconazole

Unit dose blister
14 Capsules

Rx Only

Package/Label Display Panel - CRESEMBA for injection 372 mg – individual vial carton label

NDC 0469-0420-01

CRESEMBA®
(isavuconazonium sulfate) for injection

372 mg*

*equivalent to 200 mg isavuconazole

For Intravenous Infusion Only
Use an in-line filter during infusion
Carefully read the preparation and
administration instructions prior to use

Single Dose Vial

Discard unused portion

Rx Only

Package/Label Display Panel – CRESEMBA capsules 74.5 mg – blister carton label

NDC 0469-2860-35

CRESEMBA®
(isavuconazonium sulfate) capsules

74.5 mg*

*equivalent to 40 mg isavuconazole

Unit dose blister
35 Capsules

Rx Only